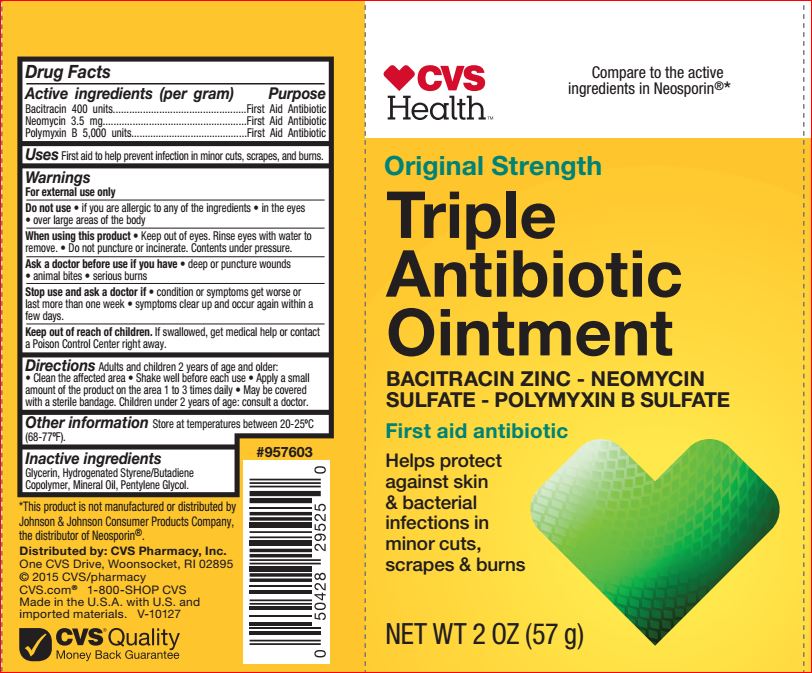 DRUG LABEL: Triple Antibiotic
NDC: 69842-047 | Form: OINTMENT
Manufacturer: CVS
Category: otc | Type: HUMAN OTC DRUG LABEL
Date: 20171120

ACTIVE INGREDIENTS: NEOMYCIN SULFATE 3.5 mg/1 g; POLYMYXIN B SULFATE 500 U/1 g; BACITRACIN 400 U/1 g
INACTIVE INGREDIENTS: Glycerin; Mineral Oil; Pentylene Glycol

Drug Facts

ACTIVE INGREDIENT

Bacitracin 400 units, Neomycin 3.5 mg, Polymyxin B 5000 units

Uses

First aid to help prevent infection and for temporary relief of pain or discomfort in minor: cuts, scrapes, and burns.

Warnings
For external use only. Do not use in the eyes, over large areas of the body. When using this product keep out of eyes. Rinse eyes with water to remove. Do not puncture or incinerate. Contents under pressure. Ask a doctor before use if you have condition or symptoms get worse or last more than one week, symptoms clear up and occur again within a few days.

Directions

Adults and children 2 years of age and older: clean the affected area, shake well before each use, spray a small amount of the product on the area 1 to 3 times daily. May be covered with a sterile bandage. Children under 2 years of age: consult a doctor.

Inactive ingredients

Glycerin, Hydrogenated Styrene/Butadiene Copolymer, Mineral Oil, Pentylene Glycol

Purpose

First aid antibiotic.

Keep out of reach of children.

If swallowed, get medical help or contact a Poison Control Center right away.